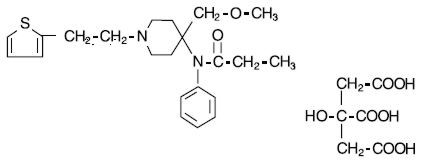 DRUG LABEL: Unknown
Manufacturer: Taylor Pharmaceuticals
Category: prescription | Type: HUMAN PRESCRIPTION DRUG LABELING
Date: 20080702
DEA Schedule: CII

SUFENTA® (SUFENTANIL CITRATE INJECTION, USP)

CII

50 mcg/mL Sufentanil base

Rx only

DESCRIPTION

SUFENTA® (sufentanil citrate) is a potent opioid analgesic chemically designated as N-[4-(methyoxymethyl)-1-[2-(2-thienyl)ethyl]-4-piperidinyl]-N-phenylpropanamide:2-hydroxy-1,2,3-propanetricarboxylate (1:1) with a molecular weight of 578.68. The structural formula of SUFENTA is:

SUFENTA is a sterile, preservative free, aqueous solution containing sufentanil citrate equivalent to 50 mcg per mL of sufentanil base for intravenous and epidural injection. The solution has a pH range of 3.5 to 6.0.

CLINICAL PHARMACOLOGY

Pharmacology

SUFENTA is an opioid analgesic. When used in balanced general anesthesia, SUFENTA has been reported to be as much as 10 times as potent as fentanyl. When administered intravenously as a primary anesthetic agent with 100% oxygen, SUFENTA is approximately 5 to 7 times as potent as fentanyl.

Assays of histamine in patients administered SUFENTA have shown no elevation in plasma histamine levels and no indication of histamine release.

(See dosage chart for more complete information on the intravenous use of SUFENTA.)

Pharmacodynamics

Intravenous use

At intravenous doses of up to 8 mcg/kg, SUFENTA is an analgesic component of general anesthesia; at intravenous doses ≥8 mcg/kg, SUFENTA produces a deep level of anesthesia. SUFENTA produces a dose related attenuation of catecholamine release, particularly norepinephrine.

At intravenous dosages of ≥8 mcg/kg, SUFENTA produces hypnosis and anesthesia without the use of additional anesthetic agents. A deep level of anesthesia is maintained at these dosages, as demonstrated by EEG patterns. Dosages of up to 25 mcg/kg attenuate the sympathetic response to surgical stress. The catecholamine response, particularly norepinephrine, is further attenuated at doses of SUFENTA of 25 to 30 mcg/kg, with hemodynamic stability and preservation of favorable myocardial oxygen balance.

SUFENTA has an immediate onset of action, with relatively limited accumulation. Rapid elimination from tissue storage sites allows for relatively more rapid recovery as compared with equipotent dosages of fentanyl. At dosages of 1 to 2 mcg/kg, recovery times are comparable to those observed with fentanyl; at dosages of >2 to 6 mcg/kg, recovery times are comparable to enflurane, isoflurane and fentanyl. Within the anesthetic dosage range of 8 to 30 mcg/kg of SUFENTA, recovery times are more rapid compared to equipotent fentanyl dosages.

The vagolytic effects of pancuronium may produce a dose dependent elevation in heart rate during SUFENTA-oxygen anesthesia. The use of moderate doses of pancuronium or of a less vagolytic neuromuscular blocking agent may be used to maintain a stable lower heart rate and blood pressure during SUFENTA-oxygen anesthesia. The vagolytic effects of pancuronium may be reduced in patients administered nitrous oxide with SUFENTA.

Preliminary data suggest that in patients administered high doses of SUFENTA, initial dosage requirements for neuromuscular blocking agents are generally lower as compared to patients given fentanyl or halothane, and comparable to patients given enflurane.

Bradycardia is infrequently seen in patients administered SUFENTA-oxygen anesthesia. The use of nitrous oxide with high doses of SUFENTA may decrease mean arterial pressure, heart rate and cardiac output.

SUFENTA at 20 mcg/kg has been shown to provide more adequate reduction in intracranial volume than equivalent doses of fentanyl, based upon requirements for furosemide and anesthesia supplementation in one study of patients undergoing craniotomy. During carotid endarterectomy, SUFENTA-nitrous oxide/oxygen produced reductions in cerebral blood flow comparable to those of enflurane-nitrous oxide/oxygen. During cardiovascular surgery, SUFENTA-oxygen produced EEG patterns similar to fentanyl-oxygen; these EEG changes were judged to be compatible with adequate general anesthesia.

The intraoperative use of SUFENTA at anesthetic dosages maintains cardiac output, with a slight reduction in systemic vascular resistance during the initial postoperative period. The incidence of postoperative hypertension, need for vasoactive agents and requirements for postoperative analgesics are generally reduced in patients administered moderate or high doses of SUFENTA as compared to patients given inhalation agents.

Skeletal muscle rigidity is related to the dose and speed of administration of SUFENTA. This muscular rigidity may occur unless preventative measures are taken (see WARNINGS).

Decreased respiratory drive and increased airway resistance occur with SUFENTA. The duration and degree of respiratory depression are dose related when SUFENTA is used at sub-anesthetic dosages. At high doses, a pronounced decrease in pulmonary exchange and apnea may be produced.

Epidural use in Labor and Delivery

Onset of analgesic effect occurs within approximately 10 minutes of administration of epidural doses of SUFENTA and bupivacaine. Duration of analgesia following a single epidural injection of 10 to 15 mcg SUFENTA and bupivacaine 0.125% averaged 1.7 hours.

During labor and vaginal delivery, the addition of 10 to 15 mcg SUFENTA to 10 mL 0.125% bupivacaine provides an increase in the duration of analgesia compared to bupivacaine without an opioid. Analgesia from 15 mcg SUFENTA plus 10 mL 0.125% bupivacaine is comparable to analgesia from 10 mL of 0.25% bupivacaine alone. Apgar scores of neonates following epidural administration of both drugs to women in labor were comparable to neonates whose mothers received bupivacaine without an opioid epidurally.

Pharmacokinetics

Intravenous use

The pharmacokinetics of intravenous SUFENTA can be described as a three-compartment model, with a distribution time of 1.4 minutes, redistribution of 17.1 minutes and elimination half-life of 164 minutes in adults. The elimination half-life of SUFENTA is shorter (e.g. 97 +/- 42 minutes) in infants and children, and longer in neonates (e.g. 434 +/- 160 minutes) compared to that of adolescents and adults. The liver and small intestine are the major sites of biotransformation. Approximately 80% of the administered dose is excreted within 24 hours and only 2% of the dose is eliminated as unchanged drug. Plasma protein binding of sufentanil, related to the alpha acid glycoprotein concentration, was approximately 93% in healthy males, 91% in mothers and 79% in neonates.

Epidural use in Labor and Delivery

After epidural administration of incremental doses totaling 5 to 40 mcg SUFENTA during labor and delivery, maternal and neonatal sufentanil plasma concentrations were at or near the 0.05 to 0.1 ng/mL limit of detection, and were slightly higher in mothers than in their infants.

CLINICAL STUDIES

Epidural use in Labor and Delivery

Epidural sufentanil was tested in 340 patients in two (one single-center and one multicenter) double-blind, parallel studies. Doses ranged from 10 to 15 mcg sufentanil and were delivered in a 10 mL volume of 0.125% bupivacaine with and without epinephrine 1:200,000. In all cases sufentanil was administered following a dose of local anesthetic to test proper catheter placement. Since epidural opioids and local anesthetics potentiate each other, these results may not reflect the dose or efficacy of epidural sufentanil by itself.

Individual doses of 10 to 15 mcg SUFENTA plus bupivacaine 0.125% with epinephrine provided analgesia during the first stage of labor with a duration of 1 to 2 hours. Onset was rapid (within 10 minutes). Subsequent doses (equal dose) tended to have shorter duration. Analgesia was profound (complete pain relief) in 80% to 100% of patients and a 25% incidence of pruritus was observed. The duration of initial doses of SUFENTA plus bupivacaine with epinephrine is approximately 95 minutes, and of subsequent doses, 70 minutes.

There are insufficient data to critically evaluate neonatal neuromuscular and adaptive capacity following recommended doses of maternally administered epidural sufentanil with bupivacaine. However, if larger than recommended doses are used for combined local and systemic analgesia, e.g. after administration of a single dose of 50 mcg epidural sufentanil during delivery, then impaired neonatal adaption to sound and light can be detected for 1 to 4 hours and if a dose of 80 mcg is used impaired neuromuscular coordination can be detected for more than 4 hours.

INDICATIONS AND USAGE

SUFENTA (sufentanil citrate) is indicated for intravenous administration in adults and pediatric patients:

as an analgesic adjunct in the maintenance of balanced general anesthesia in patients who are intubated and ventilated.

as a primary anesthetic agent for the induction and maintenance of anesthesia with 100% oxygen in patients undergoing major surgical procedures, in patients who are intubated and ventilated, such as cardiovascular surgery or neurosurgical procedures in the sitting position, to provide favorable myocardial and cerebral oxygen balance or when extended postoperative ventilation is anticipated.

SUFENTA (sufentanil citrate) is indicated for epidural administration as an analgesic combined with low dose bupivacaine, usually 12.5 mg per administration, during labor and vaginal delivery.

SEE DOSAGE AND ADMINISTRATION SECTION FOR MORE COMPLETE INFORMATION ON THE USE OF SUFENTA.

CONTRAINDICATIONS

SUFENTA is contraindicated in patients with known hypersensitivity to the drug or known intolerance to other opioid agonists.

WARNINGS

SUFENTA SHOULD BE ADMINISTERED ONLY BY PERSONS SPECIFICALLY TRAINED IN THE USE OF INTRAVENOUS AND EPIDURAL ANESTHETICS AND MANAGEMENT OF THE RESPIRATORY EFFECTS OF POTENT OPIOIDS.

AN OPIOID ANTAGONIST, RESUSCITATIVE AND INTUBATION EQUIPMENT AND OXYGEN SHOULD BE READILY AVAILABLE.

PRIOR TO CATHETER INSERTION, THE PHYSICIAN SHOULD BE FAMILIAR WITH PATIENT CONDITIONS (SUCH AS INFECTION AT THE INJECTION SITE, BLEEDING DIATHESIS, ANTICOAGULANT THERAPY, ETC.) WHICH CALL FOR SPECIAL EVALUATION OF THE BENEFIT VERSUS RISK POTENTIAL.

Intravenous use

Intravenous administration or unintentional intravascular injection during epidural administration of SUFENTA may cause skeletal muscle rigidity, particularly of the truncal muscles. The incidence and severity of muscle rigidity is dose related. Administration of SUFENTA may produce muscular rigidity with a more rapid onset of action than that seen with fentanyl. SUFENTA may produce muscular rigidity that involves the skeletal muscles of the neck and extremities. As with fentanyl, muscular rigidity has been reported to occur or recur infrequently in the extended postoperative period. The incidence of muscular rigidity associated with intravenous SUFENTA can be reduced by: 1) administration of up to 1/4 of the full paralyzing dose of a non-depolarizing neuromuscular blocking agent just prior to administration of SUFENTA at dosages of up to 8 mcg/kg, 2) administration of a full paralyzing dose of a neuromuscular blocking agent following loss of consciousness when SUFENTA is used in anesthetic dosages (above 8 mcg/kg) titrated by slow intravenous infusion, or, 3) simultaneous administration of SUFENTA and a full paralyzing dose of a neuromuscular blocking agent when SUFENTA is used in rapidly administered anesthetic dosages (above 8 mcg/kg).

The neuromuscular blocking agents used should be compatible with the patient's cardiovascular status. Adequate facilities should be available for postoperative monitoring and ventilation of patients administered SUFENTA. It is essential that these facilities be fully equipped to handle all degrees of respiratory depression.

PRECAUTIONS

General

The initial dose of SUFENTA should be appropriately reduced in elderly and debilitated patients. The effect of the initial dose should be considered in determining supplemental doses.

Vital signs should be monitored routinely.

Nitrous oxide may produce cardiovascular depression when given with high doses of SUFENTA (see CLINICAL PHARMACOLOGY).

Bradycardia has been reported infrequently with SUFENTA-oxygen anesthesia and has been responsive to atropine.

Respiratory depression caused by opioid analgesics can be reversed by opioid antagonists such as naloxone. Because the duration of respiratory depression produced by SUFENTA may last longer than the duration of the opioid antagonist action, appropriate surveillance should be maintained. As with all potent opioids, profound analgesia is accompanied by respiratory depression and diminished sensitivity to CO2 stimulation which may persist into or recur in the postoperative period. Respiratory depression may be enhanced when SUFENTA is administered in combination with volatile inhalational agents and/or other central nervous system depressants such as barbiturates, tranquilizers, and other opioids. Appropriate postoperative monitoring should be employed to ensure that adequate spontaneous breathing is established and maintained prior to discharging the patient from the recovery area. Respiration should be closely monitored following each administration of an epidural injection of SUFENTA.

Proper placement of the needle or catheter in the epidural space should be verified before SUFENTA is injected to assure that unintentional intravascular or intrathecal administration does not occur. Unintentional intravascular injection of SUFENTA could result in a potentially serious overdose, including acute truncal muscular rigidity and apnea. Unintentional intrathecal injection of the full sufentanil/bupivacaine epidural doses and volume could produce effects of high spinal anesthesia including prolonged paralysis and delayed recovery. If analgesia is inadequate, the placement and integrity of the catheter should be verified prior to the administration of any additional epidural medications. SUFENTA should be administered epidurally by slow injection.

Neuromuscular Blocking Agents

The hemodynamic effects and degree of skeletal muscle relaxation required should be considered in the selection of a neuromuscular blocking agent. High doses of pancuronium may produce increases in heart rate during SUFENTA-oxygen anesthesia. Bradycardia and hypotension have been reported with other muscle relaxants during SUFENTA-oxygen anesthesia; this effect may be more pronounced in the presence of calcium channel and/or beta-blockers. Muscle relaxants with no clinically significant effect on heart rate (at recommended doses) would not counteract the vagotonic effect of SUFENTA, therefore a lower heart rate would be expected. Rare reports of bradycardia associated with the concomitant use of succinylcholine and SUFENTA have been reported.

Interaction with Calcium Channel and Beta Blockers

The incidence and degree of bradycardia and hypotension during induction with SUFENTA may be greater in patients on chronic calcium channel and beta blocker therapy. (See Neuromuscular Blocking Agents.)

Interaction with Other Central Nervous System Depressants

Both the magnitude and duration of central nervous system and cardiovascular effects may be enhanced when SUFENTA is administered to patients receiving barbiturates, tranquilizers, other opioids, general anesthetic or other CNS depressants. In such cases of combined treatment, the dose of SUFENTA and/or these agents should be reduced.

The use of benzodiazepines with SUFENTA during induction may result in a decrease in mean arterial pressure and systemic vascular resistance.

Head Injuries

SUFENTA may obscure the clinical course of patients with head injuries.

Impaired Respiration

SUFENTA should be used with caution in patients with pulmonary disease, decreased respiratory reserve or potentially compromised respiration. In such patients, opioids may additionally decrease respiratory drive and increase airway resistance. During anesthesia, this can be managed by assisted or controlled respiration.

Impaired Hepatic or Renal Function

In patients with liver or kidney dysfunction, SUFENTA should be administered with caution due to the importance of these organs in the metabolism and excretion of SUFENTA.

Carcinogenesis, Mutagenesis and Impairment of Fertility

No long-term animal studies of SUFENTA have been performed to evaluate carcinogenic potential. The micronucleus test in female rats revealed that single intravenous doses of SUFENTA as high as 80 mcg/kg (approximately 2.5 times the upper human intravenous dose) produced no structural chromosome mutations. The Ames Salmonella typhimurium metabolic activating test also revealed no mutagenic activity. See ANIMAL TOXICOLOGY for reproduction studies in rats and rabbits.

Pregnancy Category C

SUFENTA has been shown to have an embryocidal effect in rats and rabbits when given in doses 2.5 times the upper human intravenous dose for a period of 10 days to over 30 days. These effects were most probably due to maternal toxicity (decreased food consumption with increased mortality) following prolonged administration of the drug.

No evidence of teratogenic effects have been observed after administration of SUFENTA in rats or rabbits.

Labor and Delivery

The use of epidurally administered SUFENTA in combination with bupivacaine 0.125% with or without epinephrine is indicated for labor and delivery. (See INDICATIONS AND USAGE and DOSAGE AND ADMINISTRATION sections.) SUFENTA is not recommended for intravenous use or for use of larger epidural doses during labor and delivery because of potential risks to the newborn infant after delivery. In clinical trials, one case of severe fetal bradycardia associated with maternal hypotension was reported within 8 minutes of maternal administration of sufentanil 15 mcg plus bupivacaine 0.125% (10 mL total volume).

Nursing Mothers

It is not known whether sufentanil is excreted in human milk. Because fentanyl analogs are excreted in human milk, caution should be exercised when SUFENTA is administered to a nursing woman.

Pediatric Use

The safety and efficacy of intravenous SUFENTA in pediatric patients as young as 1 day old undergoing cardiovascular surgery have been documented in a limited number of cases. The clearance of SUFENTA in healthy neonates is approximately one-half that in adults and children. The clearance rate of SUFENTA can be further reduced by up to a third in neonates with cardiovascular disease, resulting in an increase in the elimination half-life of the drug.

Animal Toxicology

The intravenous LD50 of SUFENTA is 16.8 to 18.0 mg/kg in mice, 11.8 to 13.0 mg/kg in guinea pigs and 10.1 to 19.5 mg/kg in dogs. Reproduction studies performed in rats and rabbits given doses of up to 2.5 times the upper human intravenous dose for a period of 10 to over 30 days revealed high maternal mortality rates due to decreased food consumption and anoxia, which preclude any meaningful interpretation of the results. Epidural and intrathecal injections of sufentanil in dogs and epidural injections in rats were not associated with neurotoxicity.

ADVERSE REACTIONS

The most common adverse reactions of opioids are respiratory depression and skeletal muscle rigidity, particularly of the truncal muscles. SUFENTA may produce muscular rigidity that involves the skeletal muscles of the neck and extremities. See CLINICAL PHARMACOLOGY, WARNINGS and PRECAUTIONS on the management of respiratory depression and skeletal muscle rigidity. Urinary retention has been associated with the use of epidural opioids but was not reported in the clinical trials of epidurally administered sufentanil due to the use of indwelling catheters. The incidence of urinary retention in patients without urinary catheters receiving epidural sufentanil is unknown; return of normal bladder activity may be delayed.

The following adverse reaction information is derived from controlled clinical trials in 320 patients who received intravenous sufentanil during surgical anesthesia and in 340 patients who received epidural sufentanil plus bupivacaine 0.125% for analgesia during labor and is presented below. Based on the observed frequency, none of the reactions occurring with an incidence less than 1% were observed during clinical trials of epidural sufentanil used during labor and delivery (N=340).

In general cardiovascular and musculoskeletal adverse experiences were not observed in clinical trials of epidural sufentanil. Hypotension was observed 7 times more frequently in intravenous trials than in epidural trials. The incidence of central nervous system, dermatological and gastrointestinal adverse experiences was approximately 4 to 25 times higher in studies of epidural use in labor and delivery.

Probably Causally Related: Incidence Greater than 1% - Derived from clinical trials (See preceding paragraph)

Cardiovascular: bradycardia [Incidence 3% to 9%] , hypertension, hypotension.

Musculoskeletal: chest wall rigidity.

Central Nervous System: somnolence.

Dermatological: pruritus (25%).

Gastrointestinal: nausea, vomiting.

Probably Causally Related: Incidence Less than 1% - Derived from clinical trials (Adverse events reported in post-marketing surveillance, not seen in clinical trials, are italicized.)

Body as a whole: anaphylaxis.

Cardiovascular: arrhythmia [Incidence 0.3% to 1%] , tachycardia, cardiac arrest.

Central Nervous System: chills.

Dermatological: erythema.

Musculoskeletal: skeletal muscle rigidity of neck and extremities.

Respiratory: apnea, bronchospasm, postoperative respiratory depression.

Miscellaneous: intraoperative muscle movement.

DRUG ABUSE AND DEPENDENCE

SUFENTA (sufentanil citrate) is a Schedule II controlled drug product that can produce drug dependence of the morphine type and therefore has the potential for being abused.

OVERDOSAGE

Overdosage is manifested by an extension of the pharmacological actions of SUFENTA (see CLINICAL PHARMACOLOGY) as with other potent opioid analgesics. The most serious and significant effect of overdose for both intravenous and epidural administration of SUFENTA is respiratory depression. Intravenous administration of an opioid antagonist such as naloxone should be employed as a specific antidote to manage respiratory depression. The duration of respiratory depression following overdosage with SUFENTA may be longer than the duration of action of the opioid antagonist. Administration of an opioid antagonist should not preclude more immediate countermeasures. In the event of overdosage, oxygen should be administered and ventilation assisted or controlled as indicated for hypoventilation or apnea. A patent airway must be maintained, and a nasopharyngeal airway or endotracheal tube may be indicated. If depressed respiration is associated with muscular rigidity, a neuromuscular blocking agent may be required to facilitate assisted or controlled respiration. Intravenous fluids and vasopressors for the treatment of hypotension and other supportive measures may be employed.

DOSAGE AND ADMINISTRATION

The dosage of SUFENTA should be individualized in each case according to body weight, physical status, underlying pathological condition, use of other drugs, and type of surgical procedure and anesthesia. In obese patients (more than 20% above ideal total body weight), the dosage of SUFENTA should be determined on the basis of lean body weight. Dosage should be reduced in elderly and debilitated patients (see PRECAUTIONS).

Vital signs should be monitored routinely.

Parenteral drug products should be inspected visually for particulate matter and discoloration prior to administration, whenever solution and container permit.

Because the clearance of SUFENTA is reduced in neonates, especially those with cardiovascular disease, the dose of SUFENTA should be reduced accordingly (see PRECAUTIONS).

Intravenous use

SUFENTA may be administered intravenously by slow injection or infusion 1) in doses of up to 8 mcg/kg as an analgesic adjunct to general anesthesia, and 2) in doses ≥8 mcg/kg as a primary anesthetic agent for induction and maintenance of anesthesia (see Dosage Range Chart). If benzodiazepines, barbiturates, inhalation agents, other opioids or other central nervous system depressants are used concomitantly, the dose of SUFENTA and/or these agents should be reduced (see PRECAUTIONS). In all cases dosage should be titrated to individual patient response.

Usage in Children

For induction and maintenance of anesthesia in children less than 12 years of age undergoing cardiovascular surgery, an anesthetic dose of 10 to 25 mcg/kg administered with 100% oxygen is generally recommended. Supplemental dosages of up to 25 to 50 mcg are recommended for maintenance, based on response to initial dose and as determined by changes in vital signs indicating surgical stress or lightening of anesthesia.

Premedication

The selection of preanesthetic medications should be based upon the needs of the individual patient.

Neuromuscular Blocking Agents

The neuromuscular blocking agent selected should be compatible with the patient's condition, taking into account the hemodynamic effects of a particular muscle relaxant and the degree of skeletal muscle relaxation required (see CLINICAL PHARMACOLOGY, WARNINGS and PRECAUTIONS).

ADULT DOSAGE RANGE CHART for Intravenous use
ANALGESIC COMPONENT TO GENERAL ANESTHESIA
•TOTAL DOSAGE REQUIREMENTS OF 1 MCG/KG/HR OR LESS ARE RECOMMENDED
TOTAL DOSAGE | MAINTENANCE DOSAGE
ANALGESIC DOSAGES
Incremental or Infusion: 1 to 2 mcg/kg (expected duration of anesthesia 1 to 2 hours). Approximately 75% or more of total SUFENTA dosage may be administered prior to intubation by either slow injection or infusion titrated to individual patient response. Dosages in this range are generally administered with nitrous oxide/oxygen in patients undergoing general surgery in which endotracheal intubation and mechanical ventilation are required. | Incremental: 10 to 25 mcg (0.2 to 0.5 mL) may be administered in increments as needed when movement and/or changes in vital signs indicate surgical stress or lightening of analgesia. Supplemental dosages should be individualized and adjusted to remaining operative time anticipated. Infusion: SUFENTA may be administered as an intermittent or continuous infusion as needed in response to signs of lightening of analgesia. In absence of signs of lightening of analgesia, infusion rates should always be adjusted downward until there is some response to surgical stimulation. Maintenance infusion rates should be adjusted based upon the induction dose of SUFENTA so that the total dose does not exceed 1 mcg/kg/hr of expected surgical time. Dosage should be individualized and adjusted to remaining operative time anticipated.
ANALGESIC DOSAGES
Incremental or Infusion: 2 to 8 mcg/kg (expected duration of anesthesia 2 to 8 hours). Approximately 75% or less of the total calculated SUFENTA dosage may be administered by slow injection or infusion prior to intubation, titrated to individual patient response. Dosages in this range are generally administered with nitrous oxide/oxygen in patients undergoing more complicated major surgical procedures in which endotracheal intubation and mechanical ventilation are required. At dosages in this range, SUFENTA has been shown to provide some attenuation of sympathetic reflex activity in response to surgical stimuli, provide hemodynamic stability, and provide relatively rapid recovery. | Incremental: 10 to 50 mcg (0.2 to 1 mL) may be administered in increments as needed when movement and/or changes in vital signs indicate surgical stress or lightening of analgesia. Supplemental dosages should be individualized and adjusted to the remaining operative time anticipated. Infusion: SUFENTA may be administered as an intermittent or continuous infusion as needed in response to signs of lightening of analgesia. In the absence of signs of lightening of analgesia, infusion rates should always be adjusted downward until there is some response to surgical stimulation. Maintenance infusion rates should be adjusted based upon the induction dose of SUFENTA so that the total dose does not exceed 1 mcg/kg/hr of expected surgical time. Dosage should be individualized and adjusted to remaining operative time anticipated.
ANESTHETIC DOSAGES
Incremental or Infusion: 8 to 30 mcg/kg (anesthetic doses). At this anesthetic dosage range SUFENTA is generally administered as a slow injection, as an infusion, or as an injection followed by an infusion. SUFENTA with 100% oxygen and a muscle relaxant has been found to produce sleep at dosages ≥8 mcg/kg and to maintain a deep level of anesthesia without the use of additional anesthetic agents. The addition of N2O to these dosages will reduce systolic blood pressure. At dosages in this range of up to 25 mcg/kg, catecholamine release is attenuated. Dosages of 25 to 30 mcg/kg have been shown to block sympathetic response including catecholamine release. High doses are indicated in patients undergoing major surgical procedures, in which endotracheal intubation and mechanical ventilation are required, such as cardiovascular surgery and neurosurgery in the sitting position with maintenance of favorable myocardial and cerebral oxygen balance. Postoperative observation is essential and postoperative mechanical ventilation may be required at the higher dosage range due to extended postoperative respiratory depression. Dosage should be titrated to individual patient response. | Incremental: Depending on the initial dose, maintenance doses of 0.5 to 10 mcg/kg may be administered by slow injection in anticipation of surgical stress such as incision, sternotomy or cardiopulmonary bypass. Infusion: SUFENTA may be administered by continuous or intermittent infusion as needed in response to signs of lightening of anesthesia. In the absence of lightening of anesthesia, infusion rates should always be adjusted downward until there is some response to surgical stimulation. The maintenance infusion rate for SUFENTA should be based upon the induction dose so that the total dose for the procedure does not exceed 30 mcg/kg.

In patients administered high doses of SUFENTA, it is essential that qualified personnel and adequate facilities are available for the management of postoperative respiratory depression.

Also see WARNINGS and PRECAUTIONS sections.

For purposes of administering small volumes of SUFENTA accurately, the use of a tuberculin syringe or equivalent is recommended.

Epidural use in Labor and Delivery

Proper placement of the needle or catheter in the epidural space should be verified before SUFENTA is injected to assure that unintentional intravascular or intrathecal administration does not occur. Unintentional intravascular injection of SUFENTA could result in a potentially serious overdose, including acute truncal muscular rigidity and apnea. Unintentional intrathecal injection of the full sufentanil, bupivacaine epidural doses and volume could produce effects of high spinal anesthesia including prolonged paralysis and delayed recovery. If analgesia is inadequate, the placement and integrity of the catheter should be verified prior to the administration of any additional epidural medications. SUFENTA should be administered by slow injection. Respiration should be closely monitored following each administration of an epidural injection of SUFENTA.

Dosage for Labor and Delivery: The recommended dosage is SUFENTA 10 to 15 mcg administered with 10 mL bupivacaine 0.125% with or without epinephrine. SUFENTA and bupivacaine should be mixed together before administration. Doses can be repeated twice (for a total of three doses) at not less than one-hour intervals until delivery.

HOW SUPPLIED

SUFENTA (Sufentanil Citrate Injection, USP) is supplied as a sterile aqueous preservative-free solution for intravenous and epidural use as:

NDC 11098-050-01 50 mcg/mL sufentanil base, 1 mL ampules in packages of 10
NDC 11098-050-02 50 mcg/mL sufentanil base, 2 mL ampules in packages of 10
NDC 11098-050-05 50 mcg/mL sufentanil base, 5 mL ampules in packages of 10

STORAGE

Store at 20° to 25°C (68° to 77°F). [See USP Controlled Room Temperature]. PROTECT FROM LIGHT.

U.S. Patent No. 3,998,834

MAY 1995, SEPTEMBER 1995

TAYLOR PHARMACEUTICALS
AN AKORN COMPANY
Decatur, IL 62522

SFA0N

Rev. 07/07